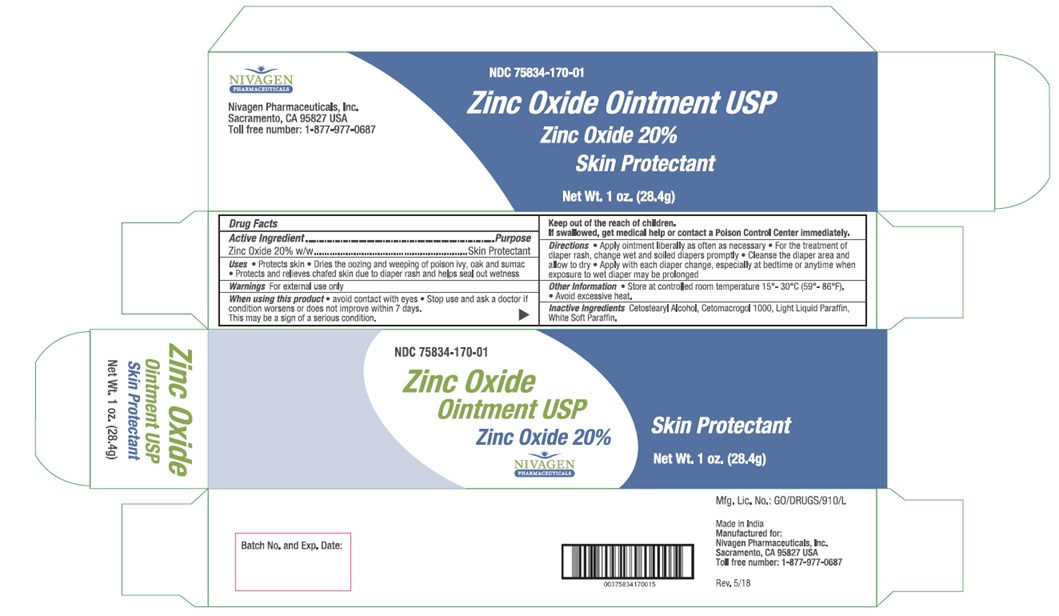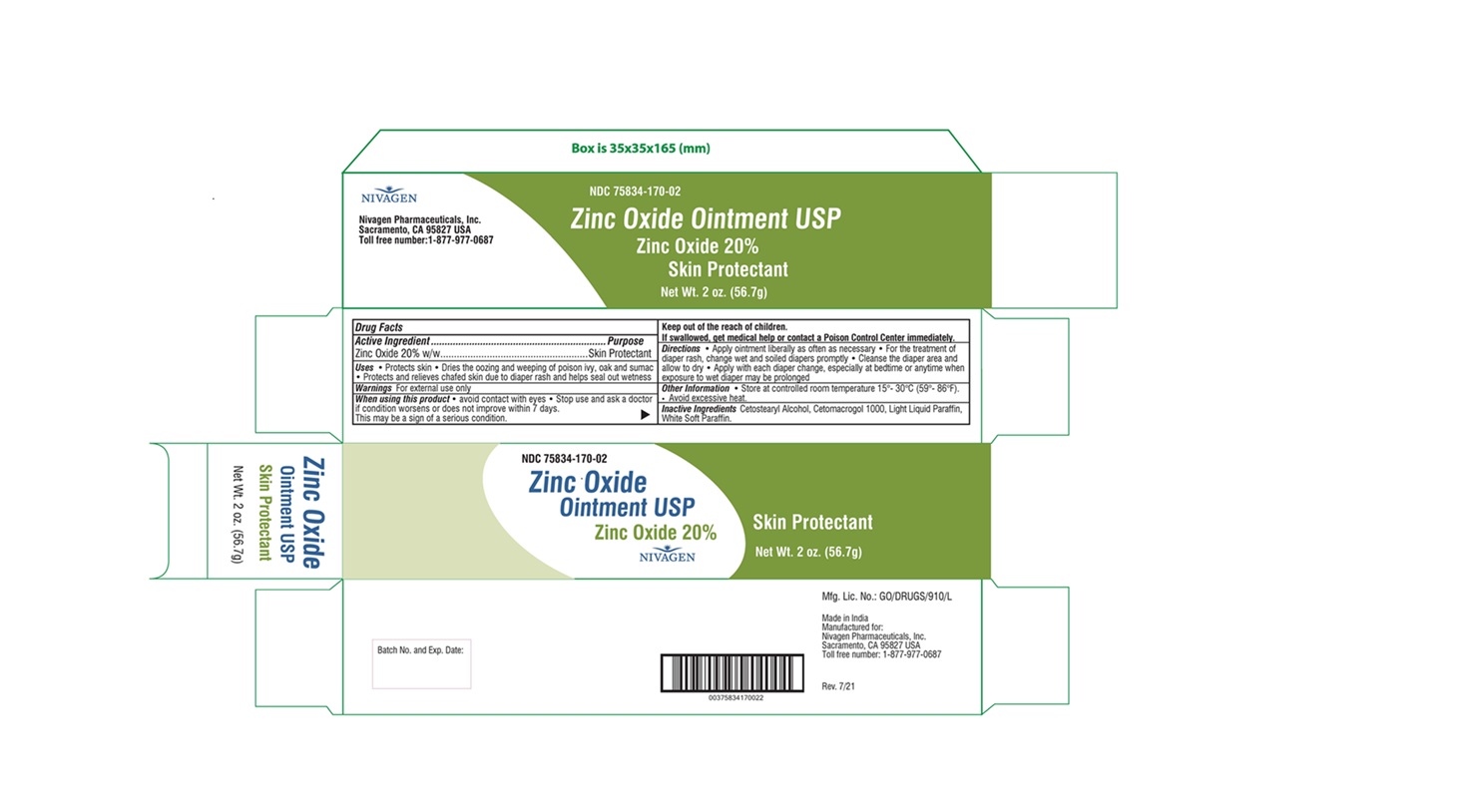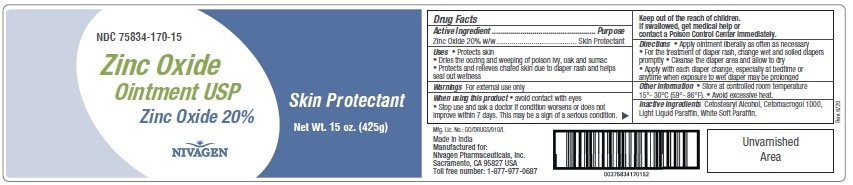 DRUG LABEL: NIVAGEN ZINC OXIDE
NDC: 75834-170 | Form: OINTMENT
Manufacturer: Nivagen Pharmaceuticals, Inc.
Category: otc | Type: Human OTC Drug Label
Date: 20250203

ACTIVE INGREDIENTS: ZINC OXIDE 200 mg/1 g
INACTIVE INGREDIENTS: CETOSTEARYL ALCOHOL; CETETH-20; PETROLATUM; LIGHT MINERAL OIL

Zinc Oxide Ointment USP
Drug Facts

Active Ingredient

Zinc Oxide 20% w/w

Purpose

Skin Protectant

Uses

• Protects skin
• Dries the oozing and weeping of poison ivy, oak and sumac
• Protects and relieves chafed skin due to diaper rash and helps seal out wetness

Warnings

For external use only

When using this product

• avoid contact with eyes
• Stop use and ask a doctor if condition worsens or does not improve within 7 days.
This may be a sign of a serious condition.

Keep out of reach of children.

If swallowed, get medical help or contact a Poison Control Center immediately.

Directions

• Apply ointment liberally as often as necessary
• For the treatment of diaper rash, change wet and soiled diapers promptly
• Cleanse the diaper area and allow to dry
• Apply with each diaper change, especially at bedtime or anytime when exposure to wet diaper may be prolonged

Other Information

• Store at controlled room temperature 15°- 30°C (59°- 86°F).
• Avoid excessive heat.

Inactive Ingredients

Cetostearyl Alcohol, Cetomacrogol 1000, Light Liquid Paraffin, White Soft Paraffin.

PRINCIPAL DISPLAY PANEL

NDC 75834-170-01
Zinc Oxide Ointment USP
Zinc Oxide 20%
Skin Protectant
Net Wt. 1 oz. (28.4 g)
Nivagen Pharmaceuticals

NDC 75834-170-02
Zinc Oxide Ointment USP
Zinc Oxide 20%
Skin Protectant
Net Wt. 2 oz. (56.7 g)
Nivagen

NDC 75834-170-15
Zinc Oxide Ointment USP
Zinc Oxide 20%
Skin Protectant
Net Wt. 15 oz. (425 g)
Nivagen